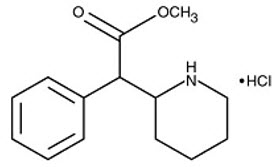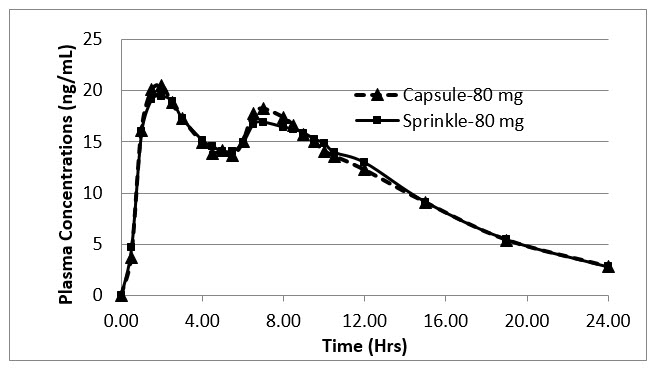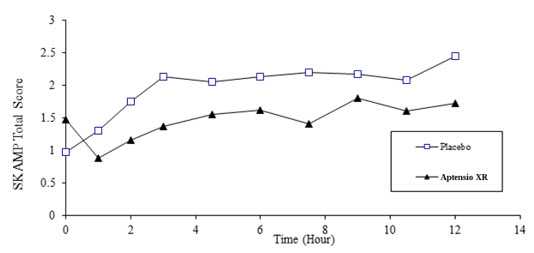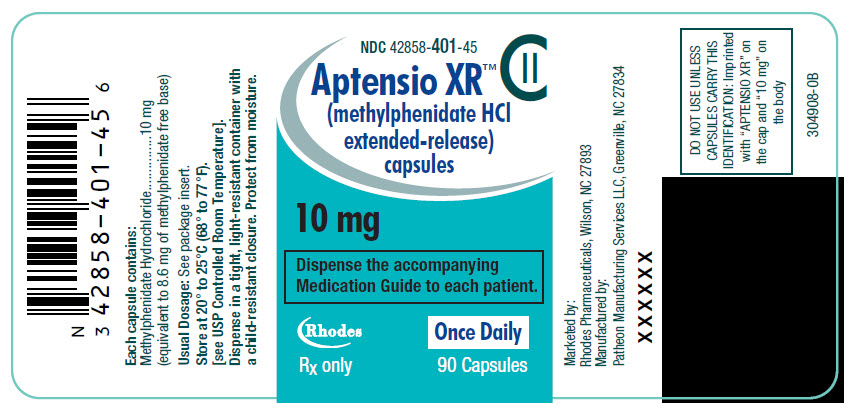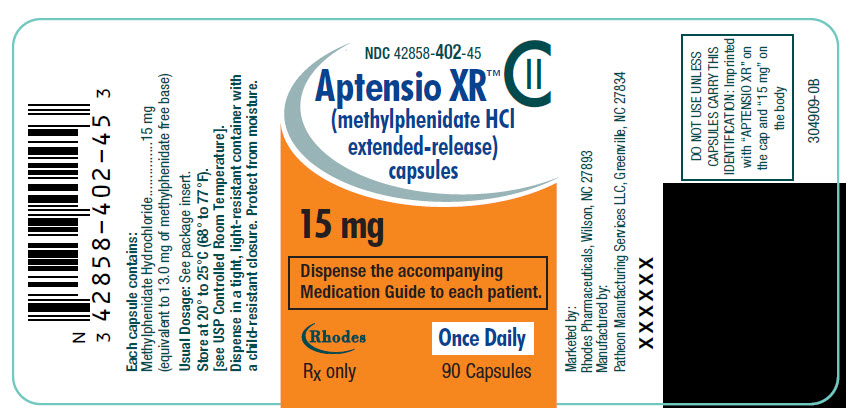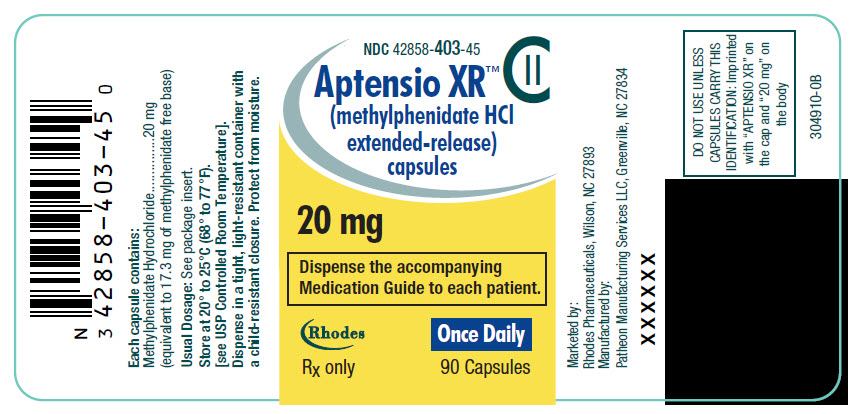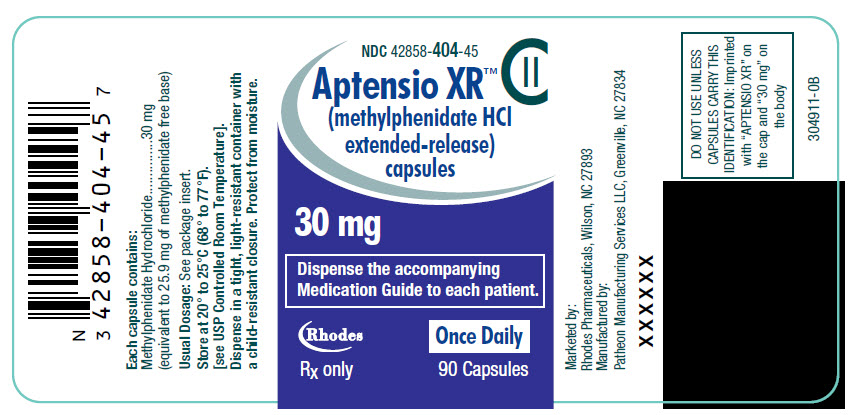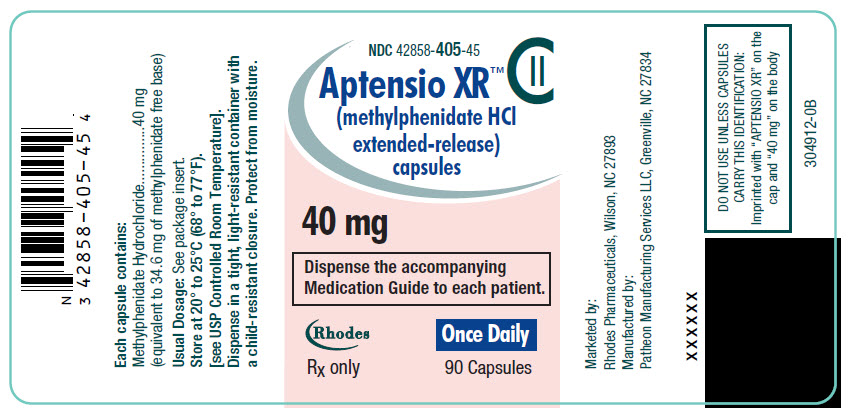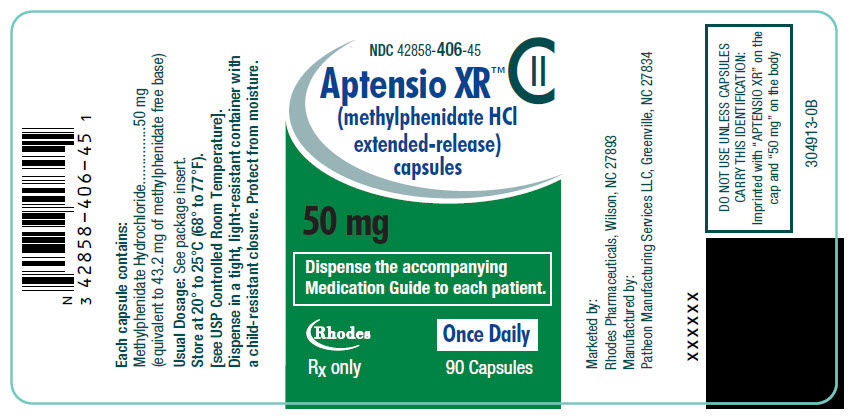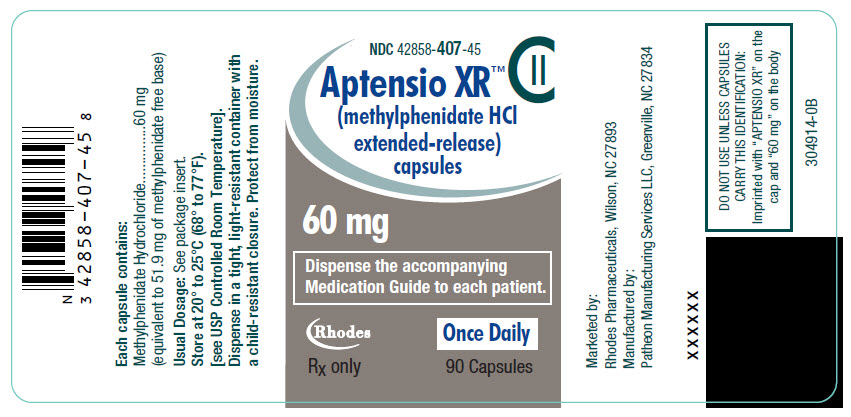 DRUG LABEL: APTENSIO XR
NDC: 42858-401 | Form: CAPSULE, EXTENDED RELEASE
Manufacturer: Rhodes Pharmaceuticals L.P.
Category: prescription | Type: HUMAN PRESCRIPTION DRUG LABEL
Date: 20250925
DEA Schedule: CII

ACTIVE INGREDIENTS: METHYLPHENIDATE HYDROCHLORIDE 10 mg/1 1
INACTIVE INGREDIENTS: SUCROSE; STARCH, CORN; HYPROMELLOSE, UNSPECIFIED; POLYETHYLENE GLYCOL, UNSPECIFIED; AMMONIO METHACRYLATE COPOLYMER TYPE B; METHACRYLIC ACID AND ETHYL ACRYLATE COPOLYMER; TRIETHYL CITRATE; TALC; WATER; SILICON DIOXIDE; FD&C BLUE NO. 1; TITANIUM DIOXIDE; GELATIN, UNSPECIFIED

HIGHLIGHTS OF PRESCRIBING INFORMATION

These highlights do not include all the information needed to use APTENSIO XR® safely and effectively. See full prescribing information for APTENSIO XR®.
APTENSIO XR® (methylphenidate hydrochloride extended-release) capsules, for oral use, CII
Initial U.S. Approval: 1955

WARNING: ABUSE, MISUSE, AND ADDICTION

See full prescribing information for complete boxed warning.

Aptensio XR has a high potential for abuse and misuse, which can lead to the development of a substance use disorder, including addiction. Misuse and abuse of CNS stimulants, including APTENSIO XR, can result in overdose and death (5.1, 9.2, 10):

- Before prescribing APTENSIO XR, assess each patient's risk for abuse, misuse, and addiction.
- Educate patients and their families about these risks, proper storage of the drug, and proper disposal of any unused drug.
- Throughout treatment, reassess each patient's risk and frequently monitor for signs and symptoms of abuse, misuse, and addiction.

RECENT MAJOR CHANGES

Indications and Usage (1) | 09/2025
Warnings and Precautions (5.7) | 09/2025

1 INDICATIONS AND USAGE

APTENSIO XR is a central nervous system (CNS) stimulant indicated for the treatment of Attention Deficit Hyperactivity Disorder (ADHD) in patients 6 years and older. (1)

Limitations of Use:

The use of Aptensio XR is not recommended in pediatric patients younger than 6 years of age because they had higher plasma exposure and a higher incidence of adverse reactions (e.g., weight loss) than patients 6 years and older at the same dosage. (5.7, 8.4)

2 DOSAGE AND ADMINISTRATION

- Recommended starting dose for patients 6 years and older: 10 mg once daily with or without food in the morning. Dosage may be increased weekly in increments of 10 mg per day. Daily dosage above 60 mg is not recommended. (2.1)
- Capsules may be swallowed whole or opened and the entire contents sprinkled onto applesauce. (2.1)

3 DOSAGE FORMS AND STRENGTHS

Extended-release capsules: 10 mg, 15 mg, 20 mg, 30 mg, 40 mg, 50 mg, and 60 mg of methylphenidate hydrochloride, which is equivalent to 8.6 mg, 13.0 mg, 17.3 mg, 25.9 mg, 34.6 mg, 43.2 mg, and 51.9 mg of methylphenidate free base, respectively, per capsule. (3)

4 CONTRAINDICATIONS

- Known hypersensitivity to methylphenidate or product components. (4)
- Concurrent treatment with a monoamine oxidase inhibitor (MAOI), or use of an MAOI within the preceding 14 days. (4)

5 WARNINGS AND PRECAUTIONS

- Risks to Patients with Serious Cardiac Disease: Avoid use in patients with known structural cardiac abnormalities, cardiomyopathy, serious cardiac arrhythmias, coronary artery disease, or other serious cardiac disease. (5.2)
- Increased Blood Pressure and Heart Rate: Monitor blood pressure and pulse. (5.3)
- Psychiatric Adverse Reactions: Prior to initiating APTENSIO XR, screen patients for risk factors for developing a manic episode. If new psychotic or manic symptoms occur, consider discontinuing APTENSIO XR. (5.4)
- Priapism: If abnormally sustained or frequent and painful erections occur, patients should seek immediate medical attention. (5.5)
- Peripheral Vasculopathy, including Raynaud's Phenomenon: Careful observation for digital changes is necessary during APTENSION XR treatment. Further clinical evaluation (e.g., rheumatology referral) may be appropriate for patients who develop signs or symptoms of peripheral vasculopathy. (5.6)
- Long-Term Suppression of Growth in Pediatric Patients: Closely monitor growth (height and weight) in pediatric patients. Pediatric patients not growing or gaining height or weight as expected may need to have their treatment interrupted. (5.7)
- Acute Angle Closure Glaucoma: APTENSIO XR-treated patients considered at risk for acute angle closure glaucoma (e.g., patients with significant hyperopia) should be evaluated by an ophthalmologist. (5.8)
- Increased Intraocular Pressure (IOP) and Glaucoma: Prescribe APTENSIO XR to patients with open-angle glaucoma or abnormally increased IOP only if the benefit of treatment is considered to outweigh the risk. Closely monitor patients with a history of increased IOP or open angle glaucoma. (5.9)
- Motor and Verbal Tics, and Worsening of Tourette's Syndrome: Before initiating APTENSIO XR, assess the family history and clinically evaluate patients for tics or Tourette's syndrome. Regularly monitor patients for the emergence or worsening of tics or Tourette's syndrome. Discontinue treatment if clinically appropriate. (5.10)

6 ADVERSE REACTIONS

The most common adverse reactions in double-blind clinical trials (> 5% and twice the rate of placebo) in pediatric patients 6 to 17 years were abdominal pain, decreased appetite, headache and insomnia. (6.1)

To report SUSPECTED ADVERSE REACTIONS, contact Rhodes Pharmaceuticals at (1-888-827-0616); or FDA at 1-800-FDA-1088 or www.fda.gov/medwatch

7 DRUG INTERACTIONS

Antihypertensive Drugs: Monitor blood pressure. Adjust dosage of antihypertensive drug as needed. (7)

FULL PRESCRIBING INFORMATION

WARNING: ABUSE, MISUSE, AND ADDICTION

APTENSIO XR has a high potential for abuse and misuse, which can lead to the development of a substance use disorder, including addiction. Misuse and abuse of CNS stimulants, including APTENSIO XR, can result in overdose and death [see Overdosage (10)], and this risk is increased with higher doses or unapproved methods of administration, such as snorting or injection.

Before prescribing APTENSIO XR, assess each patient's risk for abuse, misuse, and addiction. Educate patients and their families about these risks, proper storage of the drug, and proper disposal of any unused drug. Throughout APTENSIO XR treatment, reassess each patient's risk of abuse, misuse, and addiction and frequently monitor for signs and symptoms of abuse, misuse, and addiction [see Warnings and Precautions (5.1) and Drug Abuse and Dependence (9.2)].

1 INDICATIONS AND USAGE

APTENSIO XR is indicated for the treatment of Attention Deficit Hyperactivity Disorder (ADHD) in patients 6 years and older [see Clinical Studies (14)].

Limitations of Use

The use of Aptensio XR is not recommended in pediatric patients younger than 6 years of age because they had higher plasma exposure and a higher incidence of adverse reactions(e.g., weight loss) than patients 6 years and older at the same dosage [see Warnings and Precautions (5.7), Use in Specific Populations (8.4)].

2 DOSAGE AND ADMINISTRATION

2.1 Pretreatment Screening

Prior to treating patients with APTENSIO XR, assess:

- for the presence of cardiac disease (i.e., perform a careful history, family history of sudden death or ventricular arrhythmia, and physical exam) [see Warnings and Precautions 5.2].
- the family history and clinically evaluate patients for motor or verbal tics or Tourette's syndrome before initiating APTENSIO XR [see Warnings and Precautions (5.10)].

2.2 Recommended Dosage

The recommended starting dose of APTENSIO XR in patients 6 years and older is 10 mg once daily orally in the morning with or without food. Advise patients to establish a routine pattern with regard to meals. The dose should be individualized according to the needs and response of the patient.

The dose may be titrated weekly in increments of 10 mg. Daily doses above 60 mg have not been studied and are not recommended.

2.3 Administration Instructions

APTENSIO XR may be taken whole or the capsule may be opened and the entire contents sprinkled onto applesauce. If the patient is using the sprinkled administration method, the sprinkled applesauce should be consumed immediately; it should not be stored. Patients should take the applesauce with sprinkled beads in its entirety without chewing. The dose of a single capsule should not be divided. The contents of the entire capsule should be taken, and patients should not take anything less than one capsule per day.

2.4 Dosage Reduction and Discontinuation

If paradoxical aggravation of symptoms or other adverse reactions occur; the dosage should be reduced, or, if necessary, discontinue APTENSIO XR.

If improvement is not observed after appropriate dosage adjustment over a one-month period, discontinue APTENSIO XR.

3 DOSAGE FORMS AND STRENGTHS

- 10 mg Extended-Release Capsules – light turquoise blue cap/white body
  (imprinted with "APTENSIO XR" on cap and "10 mg" on the body)
- 15 mg Extended-Release Capsules – orange cap/white body
  (imprinted with "APTENSIO XR" on cap and "15 mg" on the body)
- 20 mg Extended-Release Capsules – yellow cap/white body
  (imprinted with "APTENSIO XR" on cap and "20 mg" on the body)
- 30 mg Extended-Release Capsules – blue violet cap/white body
  (imprinted with "APTENSIO XR" on cap and "30 mg" on the body)
- 40 mg Extended-Release Capsules – pink cap/white body
  (imprinted with "APTENSIO XR" on cap and "40 mg" on the body)
- 50 mg Extended-Release Capsules – green cap/white body
  (imprinted with "APTENSIO XR" on cap and "50 mg" on the body)
- 60 mg Extended-Release Capsules – gray cap/white body
  (imprinted with "APTENSIO XR" on cap and "60 mg" on the body)

4 CONTRAINDICATIONS

- Hypersensitivity to methylphenidate or other components of the product. Hypersensitivity reactions such as angioedema and anaphylactic reactions have been reported in patients treated with methylphenidate products [see Adverse Reactions (6.1)].
- Concomitant treatment with monoamine oxidase inhibitors, and also within 14 days following discontinuation of treatment with a monoamine oxidase inhibitor, because of the risk of hypertensive crisis [see Drug Interactions (7.1)].

5 WARNINGS AND PRECAUTIONS

5.1 Abuse, Misuse, and Addiction

APTENSIO XR has a high potential for abuse and misuse. The use of APTENSIO XR exposes individuals to the risks of abuse and misuse, which can lead to the development of a substance use disorder, including addiction. APTENSIO XR can be diverted for non-medical use into illicit channels or distribution [see Drug Abuse and Dependence (9.2)]. Misuse and abuse of CNS stimulants, including APTENSIO XR, can result in overdose and death [see Overdosage (10)], and this risk is increased with higher doses or unapproved methods of administration, such as snorting or injection.

Before prescribing APTENSIO XR, assess each patient's risk for abuse, misuse, and addiction. Educate patients and their families about these risks and proper disposal of any unused drug. Advise patients to store APTENSIO XR in a safe place, preferably locked, and instruct patients to not give APTENSIO XR to anyone else. Throughout APTENSIO XR treatment, reassess each patient's risk of abuse, misuse, and addiction and frequently monitor for signs and symptoms of abuse, misuse, and addiction.

5.2 Risks to Patients with Serious Cardiac Disease

Sudden death has been reported in patients with structural cardiac abnormalities or other serious cardiac disease who were treated with CNS stimulants at the recommended ADHD dosage.

Avoid APTENSIO XR use in patients with known structural cardiac abnormalities, cardiomyopathy, serious heart arrhythmia, coronary artery disease, or other serious cardiac disease.

5.3 Increased Blood Pressure and Heart Rate

CNS stimulants cause an increase in blood pressure (mean increase approximately 2 to 4 mmHg) and heart rate (mean increase approximately 3 to 6 bpm). Some patients may have larger increases.

Monitor all APTENSIO XR-treated patients for hypertension and tachycardia.

5.4 Psychiatric Adverse Reactions

Exacerbation of Pre-Existing Psychosis

CNS stimulants may exacerbate symptoms of behavior disturbance and thought disorder in patients with a pre-existing psychotic disorder.

Induction of a Manic Episode in Patients with Bipolar Disorder

CNS stimulants may induce a manic or mixed episode in patients. Prior to initiating APTENSIO XR treatment, screen patients for risk factors for developing a manic episode (e.g., comorbid or history of depressive symptoms or a family history of suicide, bipolar disorder, or depression).

New Psychotic or Manic Symptoms

CNS stimulants, at the recommended dosage, may cause psychotic or manic symptoms (e.g., hallucinations, delusional thinking, or mania) in patients without a prior history of psychotic illness or mania. In a pooled analysis of multiple short-term, placebo-controlled studies of CNS stimulants, psychotic or manic symptoms occurred in approximately 0.1% of CNS stimulant-treated patients, compared to 0% of placebo-treated patients. If such symptoms occur, consider discontinuing APTENSIO XR.

5.5 Priapism

Prolonged and painful erections, sometimes requiring surgical intervention, have been reported with methylphenidate use, in both adult and pediatric male patients. Although priapism was not reported with methylphenidate initiation, it developed after some time on methylphenidate, often subsequent to an increase in dosage. Priapism also occured during methylphenidate withdrawal (drug holidays or during discontinuation).

APTENSIO XR patients who develop abnormally sustained or frequent and painful erections should seek immediate medical attention.

5.6 Peripheral Vasculopathy, including Raynaud's Phenomenon

CNS stimulants, including APTENSIO XR, used to treat ADHD are associated with peripheral vasculopathy, including Raynaud's phenomenon. Signs and symptoms are usually intermittent and mild; however, sequelae have included digital ulceration and/or soft tissue breakdown. Effects of peripheral vasculopathy, including Raynaud's phenomenon, were observed in post-marketing reports and at the therapeutic dosages of CNS stimulants in all age groups throughout the course of treatment. Signs and symptoms generally improved after dosage reduction or discontinuation of the CNS stimulant.

Careful observation for digital changes is necessary during APTENSIO XR treatment. Further clinical evaluation (e.g., rheumatology referral) may be appropriate for APTENSIO XR-treated patients who develop signs or symptoms of peripheral vasculopathy.

5.7 Long-Term Suppression of Growth in Pediatric Patients

APTENSIO XR is not approved for use and is not recommended in pediatric patients below 6 years of age [see Use in Specific Populations (8.4)].

CNS stimulants have been associated with weight loss and slowing of growth rate in pediatric patients.

Careful follow-up of weight and height in pediatric patients ages 7 to 10 years who were randomized to either methylphenidate or non-medication treatment groups over 14 months, as well as in naturalistic subgroups of newly methylphenidate-treated and non-medication treated pediatric patients over 36 months (to the ages of 10 to 13 years), suggests that pediatric patients who received methylphenidate for 7 days per week throughout the year had a temporary slowing in growth rate (on average, a total of about 2 cm less growth in height and 2.7 kg less growth in weight over 3 years), without evidence of growth rebound during this development period.

Closely monitor growth (weight and height) in APTENSIO XR-treated pediatric patients. Pediatric patients who are not growing or gaining height or weight as expected may need to have their treatment interrupted.

5.8 Acute Angle Closure Glaucoma

There have been reports of angle closure glaucoma associated with methylphenidate treatment.

Although the mechanism is not clear, APTENSIO XR-treated patients considered at risk for acute angle closure glaucoma (e.g., patients with significant hyperopia) should be evaluated by an ophthalmologist.

5.9 Increased Intraocular Pressure and Glaucoma

There have been reports of an elevation of intraocular pressure (IOP) associated with methylphenidate treatment [see Adverse Reactions (6.2)].

Prescribe APTENSIO XR to patients with open-angle glaucoma or abnormally increased IOP only if the benefit of treatment is considered to outweigh the risk. Closely monitor APTENSIO XR-treated patients with a history of abnormally increased IOP or open angle glaucoma.

5.10 Motor and Verbal Tics, and Worsening of Tourette's Syndrome

CNS stimulants, including methylphenidate, have been associated with the onset or exacerbation of motor and verbal tics. Worsening of Tourette's syndrome has also been reported [see Adverse Reactions (6.2)].

Before initiating APTENSIO XR, assess the family history and clinically evaluate patients for tics or Tourette's syndrome. Regularly monitor APTENSIO XR-treated patients for the emergence or worsening of tics or Tourette's syndrome, and discontinue treatment if clinically appropriate.

6 ADVERSE REACTIONS

The following are discussed in more detail in other sections of the labeling:

- Abuse, Misuse, and Addiction [see Boxed Warning, Warnings and Precautions (5.1), and Drug Abuse and Dependence (9.2, 9.3)]
- Hypersensitivity to Methylphenidate [see Contraindications (4)]
- Hypertensive Crisis with Concomitant Use of Monoamine Oxidase Inhibitors [see Contraindications (4) and Drug Interactions (7.1)]
- Risks to Patients with Serious Cardiac Disease [see Warnings and Precautions (5.2)]
- Increased Blood Pressure and Heart Rate [see Warnings and Precautions (5.3)]
- Psychiatric Adverse Reactions [see Warnings and Precautions (5.4)]
- Priapism [see Warnings and Precautions (5.5)]
- Peripheral Vasculopathy, including Raynaud's Phenomenon [see Warnings and Precautions (5.6)]
- Long-Term Suppression of Growth in Pediatric Patients [see Warnings and Precautions (5.7)]
- Acute Angle Closure Glaucoma [see Warnings and Precautions (5.8)]
- Increased Intraocular Pressure and Glaucoma [see Warnings and Precautions (5.9)]
- Motor and Verbal Tics, and Worsening of Tourette's Syndrome [see Warnings and Precautions (5.10)]

6.1 Clinical Trials Experience

Because clinical trials are conducted under widely varying conditions, adverse reaction rates observed in the clinical trials of a drug cannot be directly compared to rates in the clinical trials of another drug and may not reflect the rates observed in clinical practice.

Adverse Reactions in Studies with Other Methylphenidate Products in Children, Adolescents, and Adults with ADHD

Commonly reported (≥2% of the methylphenidate group and at least twice the rate of the placebo group) adverse reactions from placebo-controlled trials of methylphenidate products include: decreased appetite, decreased weight, nausea, abdominal pain, dyspepsia, dry mouth, vomiting, insomnia, anxiety, nervousness, restlessness, affect lability, agitation, irritability, dizziness, vertigo, tremor, blurred vision, increased blood pressure, increased heart rate, tachycardia, palpitations, hyperhidrosis, and pyrexia.

Adverse Reactions in Studies with APTENSIO XR in Pediatric Patients with ADHD

The safety data in this section is based on data from two one-week controlled clinical studies of APTENSIO XR in pediatric patients with ADHD, one in children ages 6 to 12 years (RP-BP-EF001, hereafter "Study 1"), and one in children and adolescents ages 6 to 17 years (RP-BP-EF002, hereafter "Study 2").

Two APTENSIO XR clinical studies evaluated a total of 256 patients with ADHD. Two hundred and forty-three (243) patients participated in the double-blind phase of these two clinical studies.

Study 1 was a randomized, double-blind, single center, placebo-controlled, flexible-dose, cross-over study to evaluate the time of onset, duration of efficacy, tolerability and safety of APTENSIO XR 15 mg, 20 mg, 30 mg, or 40 mg administered for one week in 26 pediatric patients aged 6 to 12 years who met DSM-IV criteria for ADHD [see Clinical Studies (14)].

Most Common Adverse Reactions (incidence of ≥ 5% and at a rate at least twice placebo): abdominal pain, pyrexia and headache.

Adverse Reactions Leading to Discontinuation: No subjects discontinued due to adverse reactions during the double-blind phase of this study.

Study 2 was a randomized, double-blind, multicenter, placebo-controlled, parallel group, fixed-dose study of 10 mg, 15 mg, 20 mg, and 40 mg of APTENSIO XR administered for one week in 221 pediatric patients (6 to 17 years of age) who met DSM-IV criteria for ADHD [see Clinical Studies (14)].

Most Common Adverse Reactions (incidence of ≥ 5% and at a rate of at least twice placebo): abdominal pain, decreased appetite, headache and insomnia.

Adverse Reactions Leading to Discontinuation: Two patients (4.4%) in the APTENSIO XR 40 mg group discontinued due to insomnia, nausea and rapid heart rate, respectively during the double-blind phase of the study.

Table 1: Common Adverse Reactions Occurring in ≥ 2% of Pediatric Patients (6 to 17 years of age) with ADHD Taking APTENSIO XR and at a Rate Greater than Placebo (Study 2)
System Organ Class Adverse Reaction | Aptensio XR (n=183) | Placebo (n=47)
Nervous System Disorders
Headache | 10.9% | 8.5%
Insomnia | 9.8% | 2.1%
Dizziness | 2.2% | 2.1%
Gastrointestinal Disorders
Abdominal pain upper | 8.2% | 0%
Nausea | 3.8% | 2.1%
Vomiting | 3.8% | 0%
Metabolism and Nutritional
Decreased Appetite | 4.9% | 0%

6.2 Post-Marketing Experience

The following adverse reactions have been identified during post approval use of methylphenidate products. Because these reactions are reported voluntarily from a population of uncertain size, it is not possible to reliably estimate their frequency or establish a causal relationship to drug exposure. These adverse reactions are as follows:

Blood and Lymphatic System Disorders: Pancytopenia, Thrombocytopenia, Thrombocytopenic purpura

Cardiac Disorders: Angina pectoris, Bradycardia, Extrasystole, Supraventricular tachycardia, Ventricular extrasystole

Eye Disorders: Diplopia, Increased intraocular pressure, Mydriasis, Visual impairment

General Disorders: Chest pain, Chest discomfort, Hyperpyrexia

Immune System Disorders: Hypersensitivity reactions such as Angioedema, Anaphylactic reactions, Auricular swelling, Bullous conditions, Exfoliative conditions, Urticarias, Pruritus NEC, Rashes, Eruptions, and Exanthems NEC

Investigations: Alkaline phosphatase increased, Bilirubin increased, Hepatic enzyme increased, Platelet count decreased, White blood cell count abnormal, severe hepatic injury

Musculoskeletal, Connective Tissue and Bone Disorders: Arthralgia, Myalgia, Muscle twitching, Rhabdomyolysis

Nervous System: Convulsion, Grand mal convulsion, Dyskinesia, serotonin syndrome in combination with serotonergic drugs, Motor and Verbal Tics

Psychiatric Disorders: Disorientation, Libido changes

Skin and Subcutaneous Tissue Disorders: Alopecia, Erythema

7 DRUG INTERACTIONS

7.1 Clinically Important Interactions with APTENSIO XR

Monoamine Oxidase Inhibitors (MAOIs)

Do not administer APTENSIO XR concomitantly or within 14 days after discontinuing MAOI treatment. Concomitant use of MAOIs and CNS stimulants can cause hypertensive crisis. Potential outcomes include death, stroke, myocardial infarction, aortic dissection, ophthalmological complications, eclampsia, pulmonary edema, and renal failure [see Contraindications (4)].

Antihypertensive Drugs

Aptensio XR may decrease the effectiveness of drugs used to treat hypertension. Monitor blood pressure and adjust the dosage of the antihypertensive drug as needed [see Warnings and Precautions (5.3)].

Halogenated Anesthetics

Concomitant use of halogenated anesthetics and APTENSIO XR may increase the risk of sudden blood pressure and heart rate increase during surgery. Avoid use of APTENSIO XR in patients being treated with anesthetics on the day of surgery.

Risperidone

Combined use of methylphenidate with risperidone when there is a change, whether an increase or decrease, in dosage of either or both medications, may increase the risk of extrapyramidal symptoms (EPS). Monitor for signs of EPS.

8 USE IN SPECIFIC POPULATIONS

8.1 Pregnancy

Pregnancy Exposure Registry

There is a pregnancy exposure registry that monitors pregnancy outcomes in women exposed to APTENSIO XR during pregnancy. Healthcare providers are encouraged to register patients by calling the National Pregnancy Registry for Psychostimulants at 1-866-961-2388.

Risk Summary

Limited published studies report on the use of methylphenidate in pregnant women; however, the data are insufficient to inform any drug-associated risks. No effects on morphological development were observed in embryo-fetal development studies with oral administration of methylphenidate to pregnant rats and rabbits during organogenesis at doses up to 10 and 15 times, respectively, the maximum recommended human dose (MRHD) of 60 mg/day given to adolescents on a mg/m^2 basis. However, spina bifida was observed in rabbits at a dose 52 times the MRHD given to adolescents. A decrease in pup body weight was observed in a pre- and post-natal development study with oral administration of methylphenidate to rats throughout pregnancy and lactation at the highest dose of 60 mg/kg/day (6 times the MRHD given to adolescents) [see Data]. The background risk of major birth defects and miscarriage for the indicated population are unknown. However, the background risk in the U.S. general population of major birth defects is 2% to 4% and of miscarriage is 15% to 20% of clinically recognized pregnancies.

Clinical Considerations

Fetal/Neonatal adverse reactions

CNS stimulants, such as APTENSIO XR, can cause vasoconstriction and thereby decrease placental perfusion. No fetal and/or neonatal adverse reactions have been reported with the use of therapeutic doses of methylphenidate during pregnancy; however, premature delivery and low birth weight infants have been reported in amphetamine-dependent mothers.

Data

Animal Data

In embryo-fetal development studies conducted in rats and rabbits, methylphenidate was administered orally at doses of up to 75 and 200 mg/kg/day, respectively, during the period of organogenesis. Malformations (increased incidence of fetal spina bifida) were observed in rabbits at the highest dose, which is approximately 52 times the maximum recommended human dose (MRHD) of 60 mg/day given to adolescents on a mg/m^2 basis. The no effect level for embryo-fetal development in rabbits was 60 mg/kg/day (15 times the MRHD given to adolescents on a mg/m^2 basis). There was no evidence of morphological development effects in rats, although increased incidences of fetal skeletal variations were seen at the highest dose level (10 times the MRHD of 60 mg/day given to adolescents on a mg/m^2 basis), which was also maternally toxic. The no effect level for embryo-fetal development in rats was 25 mg/kg/day (2 times the MRHD on a mg/m^2 basis). When methylphenidate was administered to rats throughout pregnancy and lactation at doses of up to 45 mg/kg/day, offspring body weight gain was decreased at the highest dose (6 times the MRHD of 60 mg/day given to adolescents on a mg/m^2 basis), but no other effects on postnatal development were observed. The no effect level for pre- and postnatal development in rats was 15 mg/kg/day (1.5 times the MRHD given to adolescents on a mg/m^2 basis).

8.2 Lactation

Risk Summary

Limited published literature, based on breast milk sampling from five mothers, reports that methylphenidate is present in human milk, which resulted in infant doses of 0.16% to 0.7% of the maternal weight-adjusted dosage and a milk/plasma ratio ranging between 1.1 and 2.7. There are no reports of adverse effects on the breastfed infant and no effects on milk production. However, long-term neurodevelopmental effects on infants from stimulant exposure are unknown. The developmental and health benefits of breastfeeding should be considered along with the mother's clinical need for APTENSIO XR and any potential adverse effects on the breastfed infant from APTENSIO XR or from the underlying maternal condition.

Clinical Considerations

Monitor breastfeeding infants for adverse reactions, such as agitation, anorexia, and reduced weight gain.

8.4 Pediatric Use

The safety and effectiveness of APTENSIO XR have not been established in pediatric patients below the age of 6 years.

Safety and efficacy of APTENSIO XR were evaluated in a multicenter, placebo-controlled, double-blind, parallel group study in 119 children 4 to <6 years of age with ADHD followed by a 12-month open-label extension in 44 of these children. In these studies, patients experienced high rates of adverse reactions, most notably weight loss. Comparing weights prior to initiation of APTENSIO XR (in the safety and efficacy study) to weights after 12 months of treatment (in the open-label extension), 20 of 39 patients with data (50%) had lost enough weight to decrease 10 or more percentiles on a Centers for Disease Control growth chart for weight. In addition, systemic drug exposures in patients 4 to <6 years of age were higher than those observed in older children and adolescents at the same dose (2 to 3 fold higher Cmax and AUC). Therefore, the benefits of APTENSIO XR do not outweigh the risks in pediatric patients 4 to <6 years of age.

The safety and effectiveness of APTENSIO XR have been established in pediatric patients ages 6 to 17 years in two adequate and well-controlled clinical trials [see Clinical Studies (14)].

Long Term Suppression of Growth

Growth should be monitored during treatment with stimulants, including APTENSIO XR. Pediatric patients who are not growing or gaining weight as expected may need to have their treatment interrupted [see Warnings and Precautions (5.7)].

Juvenile Animal Toxicity Data

Rats treated with methylphenidate early in the postnatal period through sexual maturation demonstrated a decrease in spontaneous locomotor activity in adulthood. A deficit in acquisition of a specific learning task was observed in females only. The doses at which these findings were observed are at least 6 times the maximum recommended human dose (MRHD) of 60 mg/day given to children on a mg/m^2 basis.

In the study conducted in young rats, methylphenidate was administered orally at doses of up to 100 mg/kg/day for 9 weeks, starting early in the postnatal period (postnatal day 7) and continuing through sexual maturity (postnatal week 10). When these animals were tested as adults (postnatal weeks 13-14), decreased spontaneous locomotor activity was observed in males and females previously treated with 50 mg/kg/day (approximately 6 times the MRHD of 60 mg/day given to children on a mg/m^2 basis) or greater, and a deficit in the acquisition of a specific learning task was observed in females exposed to the highest dose (8 times the MRHD given to children on a mg/m^2 basis). The no effect level for juvenile neurobehavioral development in rats was 5 mg/kg/day (approximately 0.5 times the MRHD given to children on a mg/m^2 basis). The clinical significance of the long-term behavioral effects observed in rats is unknown.

8.5 Geriatric Use

Clinical trials of APTENSIO XR did not include any patients aged 65 years and over. In general, dose selection for an elderly patient start at the low end of the dosing range, reflecting the greater frequency of decreased hepatic, renal, or cardiac function and of concomitant disease or other drug therapy.

9 DRUG ABUSE AND DEPENDENCE

9.1 Controlled Substance

APTENSIO XR contains methylphenidate, a Schedule II controlled substance.

9.2 Abuse

APTENSIO XR has a high potential for abuse and misuse which can lead to the development of a substance use disorder, including addiction [see Warnings and Precautions (5.1)]. APTENSIO XR can be diverted for non-medical use into illicit channels or distribution.

Abuse is the intentional non-therapeutic use of a drug, even once, to achieve a desired psychological or physiological effect. Misuse is the intentional use, for therapeutic purposes, of a drug by an individual in a way other than prescribed by a health care provider or for whom it was not prescribed. Drug addiction is a cluster of behavioral, cognitive, and physiological phenomena that may include a strong desire to take the drug, difficulties in controlling drug use (e.g., continuing drug use despite harmful consequences, giving a higher priority to drug use than other activities and obligations), and possible tolerance or physical dependence.

Misuse and abuse of methylphenidate may cause increased heart rate, respiratory rate, or blood pressure; sweating; dilated pupils; hyperactivity; restlessness; insomnia; decreased appetite; loss of coordination; tremors; flushed skin; vomiting; and/or abdominal pain. Anxiety, psychosis, hostility, aggression, and suicidal or homicidal ideation have also been observed with CNS stimulants abuse and/or misuse. Misuse and abuse of CNS stimulants, including APTENSIO XR, can result in overdose and death [see Overdosage (10)], and this risk is increased with higher doses or unapproved methods of administration, such as snorting or injection.

9.3 Dependence

Physical Dependence

APTENSIO XR may produce physical dependence. Physical dependence is a state that develops as a result of physiological adaptation in response to repeated drug use, manifested by withdrawal signs and symptoms after abrupt discontinuation or a significant dose reduction of a drug.

Withdrawal signs and symptoms after abrupt discontinuation or dose reduction following prolonged use of CNS stimulants including APTENSIO XR include dysphoric mood; depression; fatigue; vivid, unpleasant dreams; insomnia or hypersomnia; increased appetite; and psychomotor retardation or agitation.

Tolerance

APTENSIO XR may produce tolerance. Tolerance is a physiological state characterized by a reduced response to a drug after repeated administration (i.e., a higher dose of a drug is required to produce the same effect that was once obtained at a lower dose).

10 OVERDOSAGE

Clinical Effects of Overdose

Overdose of CNS stimulants is characterized by the following sympathomimetic effects:

- Cardiovascular effects including tachyarrhythmias, and hypertension or hypotension. Vasospasm, myocardial infarction, or aortic dissection may precipitate sudden cardiac death. Takotsubo cardiomyopathy may develop.
- CNS effects including psychomotor agitation, confusion, and hallucinations. Serotonin syndrome, seizures, cerebral vascular accidents, and coma may occur.
- Life-threatening hyperthermia (temperatures greater than 104°F) and rhabdomyolysis may develop.

Overdose Management

Consider the possibility of multiple drug ingestion. The pharmacokinetic profile of APTENSIO XR should be considered when treating patients with overdose. Because methylphenidate has a large volume of distribution and is rapidly metabolized, dialysis is not useful. Consider contacting the Poison Help line (1-800-222-1222) or a medical toxicologist for additional overdose management recommendations.

11 DESCRIPTION

APTENSIO XR contains methylphenidate hydrochloride, a central nervous system (CNS) stimulant. APTENSIO XR capsules contain multi layered beads, which are composed of an immediate-release layer which contains approximately 40% of the methylphenidate dose, and a controlled release layer which contains approximately 60% of the methylphenidate dose. APTENSIO XR is available in seven capsule strengths. Each extended-release capsule for once-a-day oral administration contains 10 mg, 15 mg, 20 mg, 30 mg, 40 mg, 50 mg, or 60 mg of methylphenidate HCl USP, which is equivalent to 8.6 mg, 13.0 mg, 17.3 mg, 25.9 mg, 34.6 mg, 43.2 mg, or 51.9 mg of methylphenidate free base, respectively. Chemically, methylphenidate HCl is d,l (racemic) methyl α-phenyl-2-piperidineacetate hydrochloride. Its molecular formula is C14H19NO2∙HCl. Its structural formula is:

Methylphenidate hydrochloride USP is a white to off-white, odorless, fine crystalline powder. Its solutions are acid to litmus. It is freely soluble in water and in methanol, soluble in alcohol, and slightly soluble in chloroform and in acetone. Its molecular weight is 269.77.

Inactive Ingredients: ammonio methacrylate copolymer, type B; colloidal silicon dioxide (added if necessary); gelatin; hypromelloses; methacrylic acid copolymer, type C; polyethylene glycol; sugar spheres; talc; titanium oxide; and triethyl citrate.

Each strength capsule also contains colorant ingredients in the capsule shell as follows:

10 mg: FD&C Blue No. 1

15 mg: D&C Red No. 28, D&C Yellow No. 10, FD&C Red No. 40

20 mg: D&C Red No. 33, D&C Yellow No. 10

30 mg: FD&C Blue No. 1, FD&C Red No. 3

40 mg: D&C Red No. 28, FD&C Blue No. 1, FD&C Red No. 40

50 mg: D&C Yellow No. 10, FD&C Green No. 3

60 mg: Black Iron Oxide

12 CLINICAL PHARMACOLOGY

12.1 Mechanism of Action

Methylphenidate HCl is a central nervous system (CNS) stimulant. The mode of therapeutic action in ADHD is not known.

12.2 Pharmacodynamics

Methylphenidate is a racemic mixture comprised of the d- and l-isomers. The d-isomer is more pharmacologically active than the l-isomer. Methylphenidate blocks the reuptake of norepinephrine and dopamine into the presynaptic neuron and increase the release of these monoamines into the extraneuronal space.

12.3 Pharmacokinetics

Absorption

Following oral administration of APTENSIO XR in adults, plasma methylphenidate concentrations increase rapidly, reaching an initial maximum at about 2 hours, followed by gradual descending concentrations over the next 4 to 6 hours, after which a gradual increase begins, reaching a second peak at approximately 8 hours (Figure 1). The relative bioavailability of APTENSIO XR given once daily as compared to a methylphenidate immediate-release oral product given three times daily in adults is comparable. The relative bioavailability is 102%.

The pharmacokinetic profiles and parameters of methylphenidate are similar when APTENSIO XR is administered either as a whole capsule or sprinkled onto applesauce in subjects under fasting conditions (see Table 2 and Figure 1).

Table 2: The Single Dose Pharmacokinetics of d,l-Methylphenidate [d,l (racemic) methylphenidate HCl] ER Capsule and Sprinkle following an Oral Dose of 80 mg APTENSIO XR under Fasted Conditions in Healthy Adults
Pharmacokinetic Parameters | Capsule | Sprinkle
Cmax [Cmax, AUC (0-t) AUC (0-inf) presented as mean ± SD] (ng/mL) | 23.47 ± 11.4 | 21.78 ± 9.5
AUC(0-t) (ng.hr/mL) | 262.7 ± 135 | 262.9 ± 128
AUC(0-inf) (ng.hr/mL) | 258.1 ± 94.2 | 258.0 ± 84.4
Tmax (hr) [data presented as median (range)] | 2.0 | 2.0
Half-life (hr) | 5.09 | 5.43
Relative bioavailability | 102% | 101%

Figure 1: Mean d,l-Methylphenidate Plasma Concentration-Time Profiles following 80 mg Administered as Capsule and Sprinkle Dose in Healthy Adults

Metabolism and Excretion

In humans, methylphenidate is metabolized primarily via deesterification to alpha-phenyl-piperidine acetic acid (PPAA). The metabolite has little or no pharmacologic activity.

After oral dosing of radiolabeled methylphenidate in humans, about 90% of the radioactivity was recovered in urine. The main urinary metabolite was PPAA, accounting for approximately 80% of the dose.

Food Effects

Administration of APTENSIO XR with high fat meal showed a decreased or diminished second peak. A high-fat meal also increased the average Cmax of methylphenidate by about 28% and the AUC by about 19%. In the clinical trials of APTENSIO XR, it was administered without regard to meals.

Alcohol Effect

At an alcohol concentration up to 40%, there was 96% release of methylphenidate from APTENSIO XR 80 mg capsule within two hours. The results with the 80 mg capsule are considered to be representative of the other available capsules strengths.

Studies in Specific Populations

Gender

There is insufficient experience with the use of APTENSIO XR to detect gender variations in pharmacokinetics.

Race

There is insufficient experience with the use of APTENSIO XR to detect ethnic variations in pharmacokinetics.

Age

The pharmacokinetics of methylphenidate after APTENSIO XR administration was studied in pediatric patients with ADHD between 6 and 12 years of age. Following administration of APTENSIO XR, the bi-phasic plasma methylphenidate concentration profile was qualitatively similar in healthy adult volunteers and pediatric patients with ADHD. The bi-phasic profile in both groups is characterized by an early peak due to rapid absorption of the immediate-release component followed by a delayed, secondary peak due to the controlled-release component of APTENSIO XR.

Renal Insufficiency

There is no experience with the use of APTENSIO XR in patients with renal insufficiency. After oral administration of radiolabeled methylphenidate in humans, methylphenidate was extensively metabolized and approximately 80% of the radioactivity was excreted in the urine in the form of ritalinic acid metabolite. Since renal clearance is not an important route of methylphenidate clearance, renal insufficiency is expected to have little effect on the pharmacokinetics of APTENSIO XR.

Hepatic Insufficiency

There is no experience with the use of APTENSIO XR in patients with hepatic insufficiency.

13 NONCLINICAL TOXICOLOGY

13.1 Carcinogenesis, Mutagenesis, Impairment of Fertility

Carcinogenesis

In a lifetime carcinogenicity study carried out in B6C3F1 mice, methylphenidate caused an increase in hepatocellular adenomas and, in males only, an increase in hepatoblastomas, at a daily dose of approximately 60 mg/kg/day. This dose is approximately 2 times the maximum recommended human dose (MRHD) of 60 mg/day given to children on a mg/m^2 basis. Hepatoblastoma is a relatively rare rodent malignant tumor type. There was no increase in total malignant hepatic tumors. The mouse strain used is sensitive to the development of hepatic tumors, and the significance of these results to humans is unknown.

Methylphenidate did not cause any increase in tumors in a lifetime carcinogenicity study carried out in F344 rats; the highest dose used was approximately 45 mg/kg/day, which is approximately 4 times the MRHD (children) on a mg/m^2 basis.

Mutagenesis

Methylphenidate was not mutagenic in the in vitro Ames reverse mutation assay or in the in vitro mouse lymphoma cell forward mutation assay. Sister chromatid exchanges and chromosome aberrations were increased, indicative of a weak clastogenic response, in an in vitro assay in cultured Chinese Hamster Ovary (CHO) cells. Methylphenidate was negative in vivo in males and females in the mouse bone marrow micronucleus assay.

Impairment of Fertility

Methylphenidate did not impair fertility in male or female mice that were fed diets containing the drug in an 18-week Continuous Breeding study. The study was conducted at doses of up to 160 mg/kg/day, approximately 10 times the maximum recommended human dose of 60 mg/day given to adolescents on a mg/m^2 basis.

14 CLINICAL STUDIES

The efficacy of APTENSIO XR for the treatment of ADHD was established in a randomized, double-blind, single center, placebo-controlled, flexible-dose, cross-over trial in pediatric patients aged 6 to 12 years and a second randomized, double-blind, multicenter, placebo-controlled, fixed–dose trial in pediatric patients 6 to 17 years.

Pediatric Patients

A randomized, double-blind, placebo-controlled, flexible-dose, cross-over, analog classroom study (Study 1) was conducted in pediatric patients ages 6 to 12 years (N=26) who met DSM-IV-TR criteria for ADHD inattentive, hyperactive-impulsive or combined inattentive/hyperactive-impulsive subtypes.

Following a 2 to 4 week open-label dose optimization phase in which patients received flexible-dose APTENSIO XR 15 mg, 20 mg, 30 mg, or 40 mg administered once daily in the morning, patients were randomly assigned to APTENSIO XR (dose from open-label phase) or placebo. After 1-week of treatment, patients were evaluated over a period of 12 hours. Subsequently, patients were given the opposite treatment for 1-week and returned for the second evaluation. Patients could then enter an open-label extension phase for up to 21 months.

Efficacy assessments were conducted at 1, 2, 3, 4.5, 6, 7.5, 9, 10.5 and 12 hours post-dose using the Swanson, Kotkin, Agler, M. Flynn, and Pelham Total score (SKAMP). The primary efficacy endpoint was the average SKAMP Total Score, comparing APTENSIO XR to placebo. SKAMP is a validated 13-item teacher-rated scale that assesses manifestations of ADHD in a classroom setting.

The SKAMP Total Scores were statistically significantly better (lower) for APTENSIO XR than for placebo at the test day average and at all time points (1, 2, 3, 4.5, 6, 7.5, 9, 10.5 and 12 hours) post-dosing (see Figure 2).

Figure 2: Absolute SKAMP- Total Score after treatment with APTENSIO XR or Placebo (Study 1).

A randomized, double-blind, multicenter, placebo-controlled, parallel-group, fixed-dose study (Study 2) was conducted in pediatric patients age 6 to 17 years (N=230) who met DSM-IV-TR criteria for ADHD inattentive, hyperactive-impulsive or combined inattentive/hyperactive-impulsive subtypes.

The ADHD-RS-IV is an 18-item questionnaire with a score range of 0 to 54 points that measures the core symptoms of ADHD and includes both hyperactive/impulsive and inattentive subscales.

Patients were randomized to a daily morning dose of APTENSIO XR 10 mg, 15 mg, 20 mg, or 40 mg, or placebo for 1 week. An 11-week open label phase followed the double-blind phase. Patients could then enter another open-label phase for up to 21 months.

The primary efficacy endpoint was the mean decrease from baseline to the end of Week 1 in the ADHD-RS-IV Total Score. Each of the four APTENSIO XR doses (10 mg, 15 mg, 20 mg, and 40 mg/day) was compared to placebo at the end of week 1. For both the 20 mg/day and the 40 mg/day doses, APTENSIO XR was superior to placebo in reduction of the ADHD-RS-IV Total Score, but not for the 10 mg/day or the 15 mg/day doses.

A total of 221 patients completed the 1-week double-blind phase. Among those, 200 (90.5%) completed the 11-week open label phase and 173 (86.5%) patients continued into the 21-month open-label extension phase.

Table 3: Summary of Parallel-Group Study
Study Number | Treatment Group | Primary Efficacy Measure: ADHD-RS-IV Total Score
 |  | Mean Baseline Score (SD) | LS Mean Reduction from Baseline (SE) | Placebo-subtracted Difference [Difference (placebo minus drug) in least-squares mean change from baseline. Positive numbers indicate reduction (improvement).] (95% CI)
Study 2 (Pediatric) | APTENSIO XR 10 mg/day | 37.6 (8.32) | 9.1 (1.40) | 3.7 (-0.31, 7.66)
Study 2 (Pediatric) | APTENSIO XR 15 mg/day | 38.0 (8.64) | 10.3 (1.59) | 4.9 (0.63, 9.07)
Study 2 (Pediatric) | APTENSIO XR 20 mg/day [Doses that are demonstrated to be effective.] | 36.2 (8.46) | 11.4 (1.49) | 6.0 (1.92, 10.02)
Study 2 (Pediatric) | APTENSIO XR 40 mg/day | 35.6 (9.16) | 12.8 (1.49) | 7.4 (3.38, 11.45)
 | Placebo | 33.4 (11.01) | 5.4 (1.48) | --
Note: SD: standard deviation; SE: standard error; LS Mean: least-squares mean;
CI: confidence interval, not adjusted for multiple comparisons.

16 HOW SUPPLIED/STORAGE AND HANDLING

APTENSIO XR (methylphenidate hydrochloride extended-release) capsules are available as follows:

10 mg Capsules – light turquoise blue cap/white body, (imprinted with "APTENSIO XR" on cap and "10 mg" on the body)

Bottles of 90 | NDC 42858-401-45

15 mg Capsules – orange cap/white body, (imprinted with "APTENSIO XR" on cap and "15 mg" on the body)

Bottles of 90 | NDC 42858-402-45

20 mg Capsules – yellow cap/white body, (imprinted with "APTENSIO XR" on cap and "20 mg" on the body)

Bottles of 90 | NDC 42858-403-45

30 mg Capsules – blue violet cap/white body, (imprinted with "APTENSIO XR" on cap and "30 mg" on the body)

Bottles of 90 | NDC 42858-404-45

40 mg Capsules – pink cap/white body, (imprinted with "APTENSIO XR" on cap and "40 mg" on the body)

Bottles of 90 | NDC 42858-405-45

50 mg Capsules – green cap/white body, (imprinted with "APTENSIO XR" on cap and "50 mg" on the body)

Bottles of 90 | NDC 42858-406-45

60 mg Capsules – gray cap/white body, (imprinted with "APTENSIO XR" on cap and "60 mg" on the body)

Bottles of 90 | NDC 42858-407-45

Storage and Handling

APTENSIO XR (methylphenidate hydrochloride extended-release) capsules should be stored at 20°C to 25°C (68°F to 77°F) [see USP Controlled Room Temperature]. Protect from moisture.

Dispense in tight container (USP).

17 PATIENT COUNSELING INFORMATION

Advise patients to read the FDA-approved patient labeling (Medication Guide).

Abuse, Misuse, and Addiction

Educate patients and their families about the risks of abuse, misuse, and addiction of APTENSIO XR, which can lead to overdose and death, and proper disposal of any unused drug [see Warnings and Precautions (5.1),Drug Abuse and Dependence (9.2), Overdosage (10)]. Advise patients to store APTENSIO XR in a safe place, preferably locked, and instruct patients to not give APTENSIO XR to anyone else.

Dosage and Administration Instructions

Advise patients that APTENSIO XR can be taken with or without food and that they should establish a routine pattern of taking APTENSIO XR with regard to meals. For patients who take APTENSIO XR sprinkled over applesauce, the contents of the entire capsule should be consumed immediately; it should not be stored. Patients should take the applesauce with sprinkled beads in its entirety without chewing. When initiating treatment with APTENSIO XR, provide dosage escalation and administration instructions [see Dosage and Administration (2.2)].

Risks to Patients with Serious Cardiac Disease

Advise patients that there are potential risks to patient with serious cardiac disease, including sudden death, with APTENSIO XR use. Instruct patients to contact a healthcare provider immediately if they develop symptoms such as exertional chest pain, unexplained syncope, or other symptoms suggestive of cardiac disease [see Warnings and Precautions (5.2)].

Increased Blood Pressure and Heart Rate

Instruct patients that APTENSIO XR can cause elevations of their blood pressure and pulse rate [see Warnings and Precautions (5.3)].

Psychiatric Adverse Reactions

Advise patients that APTENSIO XR, at recommended doses, can cause psychotic or manic symptoms, even in patients without prior history of psychotic symptoms or mania [see Warnings and Precautions (5.4)].

Priapism

Advise patients of the possibility of painful or prolonged penile erections (priapism). Instruct them to seek immediate medical attention in the event of priapism [see Warnings and Precautions (5.5)].

Circulation problems in fingers and toes [Peripheral vasculopathy, including Raynaud's phenomenon]

Instruct patients beginning treatment with APTENSIO XR about the risk of peripheral vasculopathy, including Raynaud's Phenomenon, and associated signs and symptoms: fingers or toes may feel numb, cool, painful, and/or may change from pale, to blue, to red. Instruct patients to report to their physician any new numbness, pain, skin color change, or sensitivity to temperature in fingers or toes.

Instruct patients to call their physician immediately with any signs of unexplained wounds appearing on fingers or toes while taking APTENSIO XR. Further clinical evaluation (e.g. rheumatology referral) may be appropriate for certain patients [see Warnings and Precautions (5.6)].

Long-Term Suppression of Growth in Pediatric Patients

Advise patients that APTENSIO XR may cause slowing of growth and weight loss [see Warnings and Precautions (5.7)].

Increased Intraocular Pressure (IOP) and Glaucoma

Advise patients that IOP and glaucoma may occur during treatment with APTENSIO XR [see Warnings and Precautions (5.9)].

Motor and Verbal Tics, and Worsening of Tourette's Syndrome

Advise patients that motor and verbal tics and worsening of Tourette's syndrome may occur during treatment with APTENSIO XR. Instruct patients to notify their healthcare provider if emergence of new tics or worsening of tics or Tourette's syndrome occurs [see Warnings and Precautions (5.10)].

Alcohol Effect

Advise patients to avoid alcohol while taking APTENSIO XR. Consumption of alcohol while taking APTENSIO XR may result in a more rapid release of the dose of methylphenidate [see Clinical Pharmacology (12.3)].

Pregnancy Registry

Advise patients that there is a pregnancy exposure registry that monitors pregnancy outcomes in women exposed to APTENSIO XR during pregnancy [see Use in Specific Populations (8.1)].

Marketed by:
Rhodes Pharmaceuticals
Wilson, NC 27893

Manufactured by:
Purdue Pharma L.P.
Stamford, CT 06901

APTENSIO XR® is a trademark of Rhodes Pharmaceuticals.

This product is covered by US patents including US Patents No. 6,419,960, 7,083,808, 7,247,318, 8,580,310, 9,066,869 and 9,801,823.

xxxxxx-0x

MEDICATION GUIDE
APTENSIO XR® (App-ten-see-o)
(methylphenidate hydrochloride extended-release)
capsules, CII

What is the most important information I should know about APTENSIO XR?
APTENSIO XR may cause serious side effects, including:

- Abuse, misuse, and addiction. APTENSIO XR has a high chance for abuse and misuse and may lead to substance use problems, including addiction. Misuse and abuse of APTENSIO XR, other methylphenidate containing medicines, and amphetamine containing medicines, can lead to overdose and death. The risk of overdose and death is increased with higher doses of APTENSIO XR or when it is used in ways that are not approved, such as snorting or injection.
  - Your healthcare provider should check you or your child's risk for abuse, misuse, and addiction before starting treatment with APTENSIO XR and will monitor you or your child during treatment.
  - APTENSIO XR may lead to physical dependence after prolonged use, even if taken as directed by your healthcare provider.
  - Do not give APTENSIO XR to anyone else. See "What is APTENSIO XR?" for more information.
  - Keep APTENSIO XR in a safe place and properly dispose of any unused medicine. See "How should I store APTENSIO XR?" for more information.
  - Tell your healthcare provider if you or your child have ever abused or been dependent on alcohol, prescription medicines, or street drugs.
- Risks for people with serious heart disease. Sudden death has happened in people who have heart defects or other serious heart disease.
  Your healthcare provider should check you or your child carefully for heart problems before starting treatment with APTENSIO XR. Tell your healthcare provider if you or your child have any heart problems, heart disease, or heart defects.
  Your healthcare provider should check you or your child's blood pressure and heart rate regularly during treatment with APTENSIO XR.
  Call your healthcare provider or go the nearest hospital emergency room right away if you or your child have any signs of heart problems such as chest pain, shortness of breath, or fainting during treatment with APTENSIO XR.
- Increased blood pressure and heart rate.
  Your healthcare provider should check your or your child's blood pressure and heart rate regularly during treatment with APTENSIO XR.
- Mental (psychiatric) problems, including:
  - new or worse behavior and thought problems
  - new or worse bipolar illness
  - new psychotic symptoms (such as hearing voices, or seeing or believing things that are not real) or new manic symptoms
  Tell your healthcare provider about any mental problems you or your child have, or about a family history of suicide, bipolar illness, or depression.
  Call your healthcare provider right away if you or your child have any new or worsening mental symptoms or problems during treatment with APTENSIO XR, especially hearing voices, seeing or believing things that are not real, or new manic symptoms.

What is APTENSIO XR?

APTENSIO XR is a central nervous system (CNS) stimulant prescription medicine used for the treatment of Attention Deficit Hyperactivity Disorder (ADHD) in people 6 years of age and older. APTENSIO XR may help increase attention and decrease impulsiveness and hyperactivity in people with ADHD.

- APTENSIO XR is not recommended for use in children under 6 years of age.

APTENSIO XR is a federally controlled substance (CII) because it contains methylphenidate that can be a target for people who abuse prescription medicines or street drugs. Keep APTENSIO XR in a safe place to protect it from theft. Never give your APTENSIO XR to anyone else, because it may cause death or harm them. Selling or giving away APTENSIO XR may harm others and is against the law.

Do not take APTENSIO XR if you or your child are:

- allergic to methylphenidate hydrochloride or any of the ingredients in APTENSIO XR. See the end of this Medication Guide for a complete list of ingredients in APTENSIO XR.
- taking or have stopped taking within the past 14 days a medicine used to treat depression called a monoamine oxidase inhibitor (MAOI).

Before taking APTENSIO XR tell your healthcare provider about all medical conditions, including if you or your child:

- have heart problems, heart disease, heart defects, or high blood pressure
- have mental problems including psychosis, mania, bipolar illness, or depression, or have a family history of suicide, bipolar illness, or depression
- have circulation problems in fingers and toes
- have eye problems, including increased pressure in your eye, glaucoma, or problems with your close-up vision (farsightedness)
- have or had repeated movements or sounds (tics) or Tourette's syndrome, or have a family history of tics or Tourette's syndrome
- are pregnant or plan to become pregnant. It is not known if APTENSIO XR will harm your unborn baby.
  - There is a pregnancy registry for females who are exposed to APTENSIO XR during pregnancy. The purpose of the registry is to collect information about the health of females exposed to APTENSIO XR and their baby. If you or your child becomes pregnant during treatment with APTENSIO XR, talk to your healthcare provider about registering with the National Pregnancy Registry for Psychostimulants at 1-866-961-2388.
- are breastfeeding or plan to breastfeed. APTENSIO XR passes into breast milk. Talk to your healthcare provider about the best way to feed the baby during treatment with APTENSIO XR.

Tell your healthcare provider about all the medicines that you or your child take, including prescription and over-the-counter medicines, vitamins, and herbal supplements.
APTENSIO XR and some medicines may interact with each other and cause serious side effects. Sometimes the doses of other medicines will need to be changed during treatment with APTENSIO XR. Your healthcare provider will decide whether APTENSIO XR can be taken with other medicines.
Especially tell your healthcare provider if you or your child take a medicine used to treat depression called monoamine oxidase inhibitor (MAOI).
Know the medicines that you or your child take. Keep a list of the medicines with you to show your healthcare provider and pharmacist. Do not start any new medicine during treatment with APTENSIO XR without talking to your healthcare provider first.

How should APTENSIO XR be taken?

- Take APTENSIO XR exactly as prescribed by your healthcare provider.
- Your healthcare provider may change the dose if needed.
- Take APTENSIO XR by mouth 1 time each day in the morning.
- APTENSIO XR can be taken with or without food but take it the same way each time.
- Swallow APTENSIO XR capsules whole, or if APTENSIO XR capsules cannot be swallowed whole, the capsules may be opened and sprinkled onto a tablespoonful of applesauce. Make sure to sprinkle all the medicine onto the applesauce. The APTENSIO XR dose should not be divided.
  - swallow all the applesauce and medicine mixture without chewing right away or within 10 minutes
  - do not chew the applesauce and medicine mixture
  - do not store applesauce and medicine mixture
- If a dose of APTENSIO XR is missed, do not take the dose later in the day or take an extra dose to make up for the missed dose, wait until the next morning to take the next scheduled dose.

If you or your child take too much APTENSIO XR, call your healthcare provider or Poison Help line at 1-800-222-1222 or go to the nearest hospital emergency room right away.

What should be avoided during treatment with APTENSIO XR?
Avoid drinking alcohol during treatment with APTENSIO XR. This may cause a faster release of the APTENSIO XR medicine.

What are possible side effects of APTENSIO XR?
APTENSIO XR may cause serious side effects, including:
See "What is the most important information I should know about APTENSIO XR?"

- Painful and prolonged erections (priapism). Priapism has happened in males who take products that contain methylphenidate. If you or your child develop priapism, get medical help right away.
- Circulation problems in fingers and toes (peripheral vasculopathy, including Raynaud's phenomenon). Signs and symptoms may include:
  - fingers or toes may feel numb, cool, painful
  - fingers or toes may change color from pale, to blue, to red
  Tell your healthcare provider if you have or your child have numbness, pain, skin color change, or sensitivity to temperature in the fingers or toes.
  Call your healthcare provider right away if you have or your child have any signs of unexplained wounds appearing on fingers or toes during treatment with APTENSIO XR.
- Slowing of growth (height and weight) in children. Children should have their height and weight checked often during treatment with APTENSIO XR. APTENSIO XR treatment may be stopped if your child is not growing or gaining weight.
- Eye problems (increased pressure in the eye and glaucoma). Call your healthcare provider right away if you or your child develop changes in your vision or eye pain, swelling, or redness.
- New or worsening tics or worsening Tourette's syndrome. Tell your healthcare provider if you or your child get any new or worsening tics or worsening Tourette's syndrome during treatment with APTENSIO XR.

The most common side effects of APTENSIO XR in children 6 to 17 years of age include stomach pain, decreased appetite, headache, trouble sleeping.
These are not all the possible side effects of APTENSIO XR.
Call your doctor for medical advice about side effects. You may report side effects to FDA at 1-800-FDA-1088.
You may also report side effects to Rhodes Pharmaceuticals at 1-888-827-0616.

How should I store APTENSIO XR?

- Store APTENSIO XR at room temperature between 68°F to 77°F (20°C to 25°C).
- Store APTENSIO XR in a safe place, like a locked cabinet. Protect from moisture.
- Dispose of remaining, unused, or expired APTENSIO XR by a medicine take-back program at a U.S. Drug Enforcement Administration (DEA) authorized collection site. If no take-back program or DEA authorized collector is available, mix APTENSIO XR with an undesirable, nontoxic substance such as dirt, cat litter, or used coffee grounds to make it less appealing to children and pets. Place the mixture in a container such as a sealed plastic bag and throw away APTENSIO XR in the household trash. Visit www.fda.gov/drugdisposal for additional information on disposal of unused medicines.

Keep APTENSIO XR and all medicines out of the reach of children.

General information about the safe and effective use of APTENSIO XR.
Medicines are sometimes prescribed for purposes other than those listed in a Medication Guide. Do not use APTENSIO XR for a condition for which it was not prescribed. Do not give APTENSIO XR to other people, even if they have the same symptoms. It may harm them and it is against the law. You can ask your healthcare provider or pharmacist for information about APTENSIO XR that is written for healthcare professionals.

What are the ingredients in APTENSIO XR?
Active Ingredient: methylphenidate hydrochloride
Inactive Ingredients: ammonio methacrylate copolymer, type B; colloidal silicon dioxide (added if necessary); gelatin; hypromelloses; methacrylic acid copolymer, type C; polyethylene glycol; sugar spheres; talc; titanium oxide; and triethyl citrate.
Manufactured by: Purdue Pharma L.P., Stamford, CT 06901
For more information, call Rhodes Pharmaceuticals (the distributor for APTENSIO XR) at 1-888-827-0616.

This Medication Guide has been approved by the U.S. Food and Drug Administration.

Revised: 09/2025

PRINCIPAL DISPLAY PANEL - 10 mg Capsule Bottle Label

NDC 42858-401-45

Aptensio XR™
(methylphenidate HCl
extended-release)
capsules

CII

10 mg

Dispense the accompanying
Medication Guide to each patient.

Rhodes

Once Daily

Rx only
90 Capsules

PRINCIPAL DISPLAY PANEL - 15 mg Capsule Bottle Label

NDC 42858-402-45

Aptensio XR™
(methylphenidate HCl
extended-release)
capsules

CII

15 mg

Dispense the accompanying
Medication Guide to each patient.

Rhodes

Once Daily

Rx only
90 Capsules

PRINCIPAL DISPLAY PANEL - 20 mg Capsule Bottle Label

NDC 42858-403-45

Aptensio XR™
(methylphenidate HCl
extended-release)
capsules

CII

20 mg

Dispense the accompanying
Medication Guide to each patient.

Rhodes

Once Daily

Rx only
90 Capsules

PRINCIPAL DISPLAY PANEL - 30 mg Capsule Bottle Label

NDC 42858-404-45

Aptensio XR™
(methylphenidate HCl
extended-release)
capsules

CII

30 mg

Dispense the accompanying
Medication Guide to each patient.

Rhodes

Once Daily

Rx only
90 Capsules

PRINCIPAL DISPLAY PANEL - 40 mg Capsule Bottle Label

NDC 42858-405-45

Aptensio XR™
(methylphenidate HCl
extended-release)
capsules

CII

40 mg

Dispense the accompanying
Medication Guide to each patient.

Rhodes

Once Daily

Rx only
90 Capsules

PRINCIPAL DISPLAY PANEL - 50 mg Capsule Bottle Label

NDC 42858-406-45

Aptensio XR™
(methylphenidate HCl
extended-release)
capsules

CII

50 mg

Dispense the accompanying
Medication Guide to each patient.

Rhodes

Once Daily

Rx only
90 Capsules

PRINCIPAL DISPLAY PANEL - 60 mg Capsule Bottle Label

NDC 42858-407-45

Aptensio XR™
(methylphenidate HCl
extended-release)
capsules

CII

60 mg

Dispense the accompanying
Medication Guide to each patient.

Rhodes

Once Daily

Rx only
90 Capsules